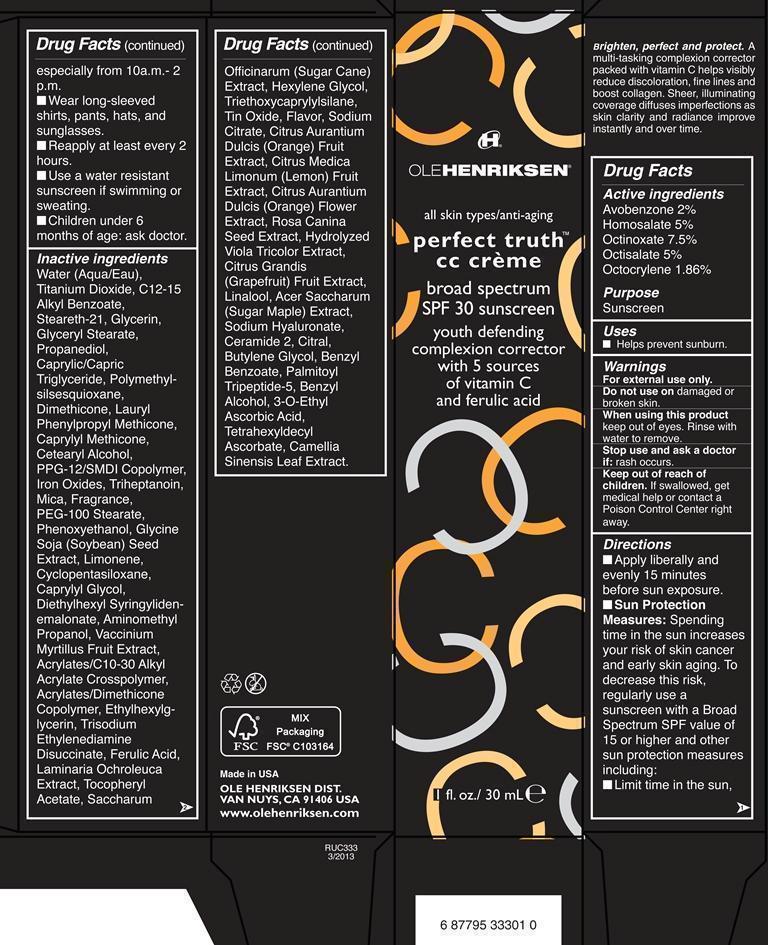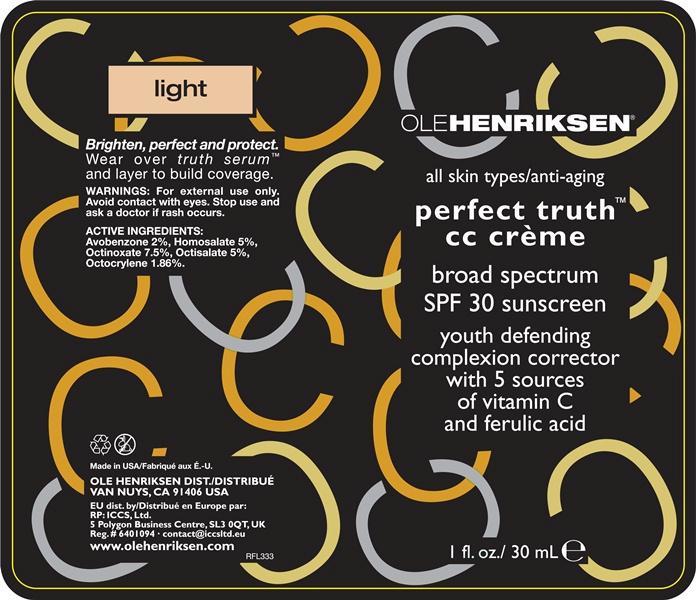 DRUG LABEL: perfect truth cc broad spectrum SPF 30 sunscreen
NDC: 51770-112 | Form: CREAM
Manufacturer: Ole Henriksen
Category: otc | Type: HUMAN OTC DRUG LABEL
Date: 20130401

ACTIVE INGREDIENTS: AVOBENZONE 2 g/100 mL; HOMOSALATE 5 g/100 mL; OCTINOXATE 7.5 g/100 mL; OCTISALATE 5 g/100 mL; OCTOCRYLENE 1.86 g/100 mL
INACTIVE INGREDIENTS: WATER; TITANIUM DIOXIDE; C12-15 ALKYL BENZOATE; STEARETH-21; GLYCERIN; GLYCERYL MONOSTEARATE; PROPANEDIOL; MEDIUM-CHAIN TRIGLYCERIDES; POLYMETHYLSILSESQUIOXANE (11 MICRONS); DIMETHICONE; CETOSTEARYL ALCOHOL; FERRIC OXIDE RED; FERRIC OXIDE YELLOW; FERROSOFERRIC OXIDE; TRIHEPTANOIN; MICA; PEG-100 STEARATE; PHENOXYETHANOL; SOYBEAN; LIMONENE, (+)-; CYCLOMETHICONE 5; CAPRYLYL GLYCOL; DIETHYLHEXYL SYRINGYLIDENEMALONATE; AMINOMETHYLPROPANOL; BILBERRY; CARBOMER COPOLYMER TYPE A (ALLYL PENTAERYTHRITOL CROSSLINKED); ETHYLHEXYLGLYCERIN; TRISODIUM ETHYLENEDIAMINE DISUCCINATE; FERULIC ACID; LAMINARIA OCHROLEUCA; .ALPHA.-TOCOPHEROL ACETATE; SUGARCANE; HEXYLENE GLYCOL; TRIETHOXYCAPRYLYLSILANE; STANNIC OXIDE; SODIUM CITRATE; ORANGE; LEMON; CITRUS SINENSIS FLOWER; ROSA CANINA SEED; PUMMELO; LINALOOL, (+)-; ACER SACCHARUM BARK/SAP; HYALURONATE SODIUM; CERAMIDE 2; CITRAL; BUTYLENE GLYCOL; BENZYL BENZOATE; PALMITOYL TRIPEPTIDE-5; BENZYL ALCOHOL; 3-O-ETHYL ASCORBIC ACID; TETRAHEXYLDECYL ASCORBATE; GREEN TEA LEAF

Perfect Truth cc Cream broad spectrum SPF 30 light

Active Ingredients purpose

Avobenzone 2% sunscreen

Homosalate 5% sunscreen

Octinoxate 7.5 % sunscreen

Octisalate 5% sunscreen

Octocrylene 1.86% sunscreen

Uses

Helps prevent sunburn

Keep out of reach of children. If swallowed, get medical help or contact a Poison Control Center right away.

Stop use and ask a doctor if: rash occurs.

Warnings

For external use only.

Do not use on damaged or broken skin.

When using this product keep out of eyes. Rinse with water to remove.

Directions

■ Apply liberally and evenly 15 minutes before sun exposure.

Sun Protection Measures:

Spending time in the sun increases your risk of skin cancer and early skin aging. To decrease this risk, regularly use a sunscreen with a Broad Spectrum SPF value of 15 or higher and other sun protection measures

including:

■ Limit time in the sun, especially from 10a.m.- 2 p.m.

■ Wear long-sleeved shirts, pants, hats, and sunglasses.

■ Reapply at least every 2 hours.

■ Use a water resistant sunscreen if swimming or sweating.

■ Children under 6 months of age: ask doctor.

INACTIVE INGREDIENT

Water (Aqua/Eau), Titanium Dioxide, C12-15 Alkyl Benzoate, Steareth-21, Glycerin, Glyceryl Stearate, Propanediol, Caprylic/Capric Triglyceride, Polymethylsilsesquioxane, Dimethicone, Lauryl Phenylpropyl Methicone, Caprylyl Methicone, Cetearyl Alcohol, PPG-12/SMDI Copolymer, Iron Oxides, Triheptanoin, Mica, Fragrance, PEG-100 Stearate, Phenoxyethanol, Glycine Soja (Soybean) Seed Extract, Limonene, Cyclopentasiloxane, Caprylyl Glycol, Diethylhexyl Syringylidenemalonate, Aminomethyl Propanol, Vaccinium Myrtillus Fruit Extract, Acrylates/C10-30 Alkyl Acrylate Crosspolymer, Acrylates/Dimethicone Copolymer, Ethylhexylglycerin, Trisodium Ethylenediamine Disuccinate, Ferulic Acid, Laminaria Ochroleuca Extract, Tocopheryl Acetate, Saccharum Officinarum (Sugar Cane) Extract, Hexylene Glycol, Triethoxycaprylylsilane, Tin Oxide, Flavor, Sodium Citrate, Citrus Aurantium Dulcis (Orange) Fruit Extract, Citrus Medica Limonum (Lemon) Fruit Extract, Citrus Aurantium Dulcis (Orange) Flower Extract, Rosa Canina Seed Extract, Hydrolyzed Viola Tricolor Extract, Citrus Grandis (Grapefruit) Fruit Extract, Linalool, Acer Saccharum (Sugar Maple) Extract, Sodium Hyaluronate, Ceramide 2, Citral, Butylene Glycol, Benzyl Benzoate, Palmitoyl Tripeptide-5, Benzyl Alcohol, 3-O-Ethyl Ascorbic Acid, Tetrahexyldecyl Ascorbate, Camellia Sinensis Leaf Extract.

PACKAGE LABEL

Ole Henriksen

all skin types/anti-aging

perfect truth cc creme

broad spectrum SPF 30 sunscreen

youth defending complexion corrector with 5 sources of vitamin C and ferulic acid

1 fl. oz./ 30 mL